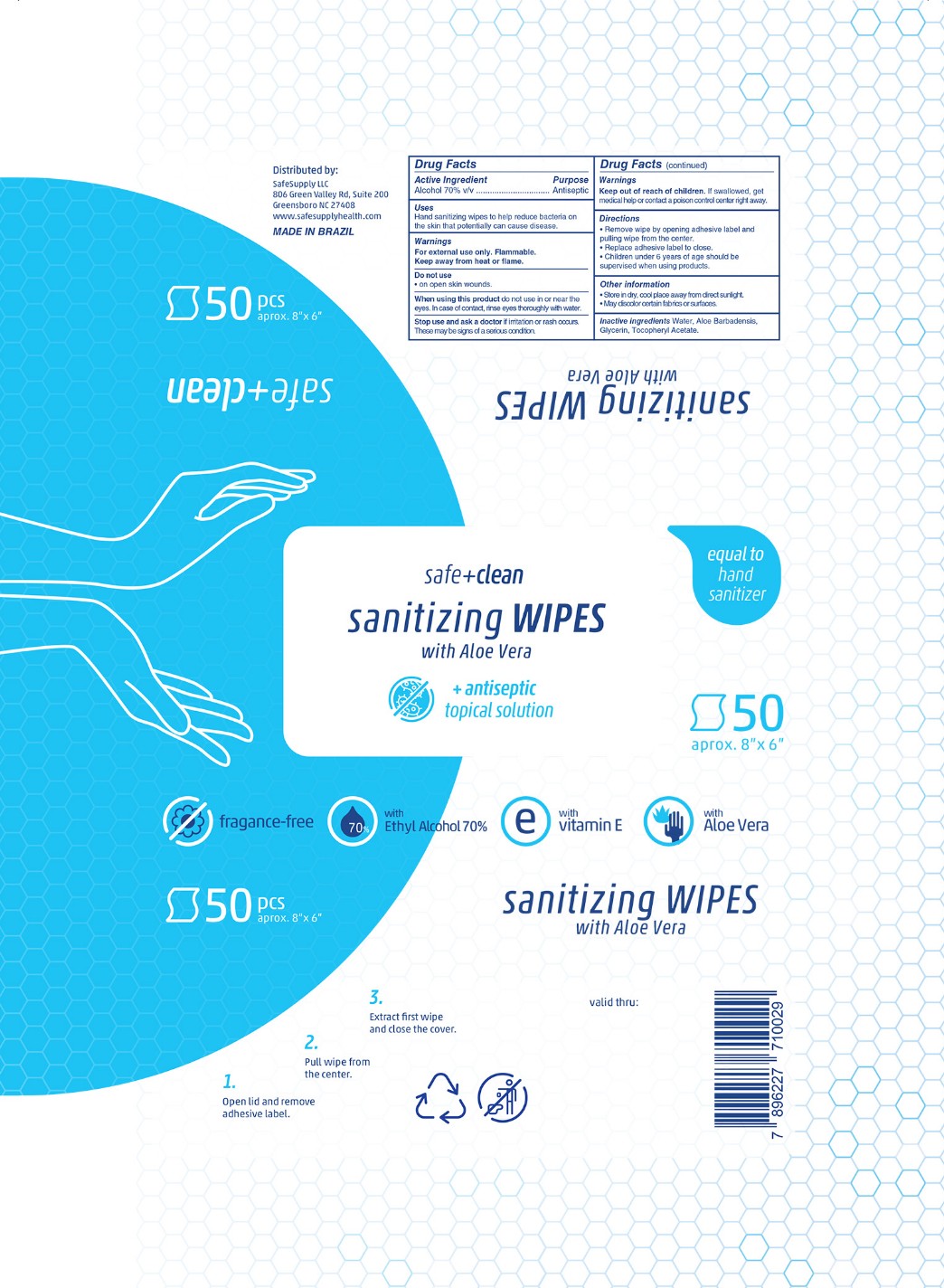 DRUG LABEL: Safe and Clean
NDC: 80467-111 | Form: CLOTH
Manufacturer: HIGIE PLUS COTTONBABY INDUSTRIA E COMERCIO LTDA
Category: otc | Type: HUMAN OTC DRUG LABEL
Date: 20201001

ACTIVE INGREDIENTS: ALCOHOL 70 mL/100 mL
INACTIVE INGREDIENTS: ALPHA-TOCOPHEROL ACETATE; GLYCERIN; ALOE VERA LEAF; WATER

HIGIE-SafeSupply Alcohol Wipes

Active Ingredient(s)

Alcohol 70% v/v. Purpose: Antiseptic

Purpose

Antiseptic, Hand Sanitizer

Use

Hand Sanitizing wipes to help reduce bacteria that potentially can cause disease.

Warnings

For external use only. Flammable. Keep away from heat or flame.

Do not use

- in children less than 2 months of age
- on open skin wounds

When using this product keep out of eyes, ears, and mouth. In case of contact with eyes, rinse eyes thoroughly with water.
Stop use and ask a doctor if irritation or rash occurs. These may be signs of a serious condition.
Keep out of reach of children. If swallowed, get medical help or contact a Poison Control Center right away.

Stop use and ask a doctor if irritation or rash occurs. These may be signs of a serious condition.

Keep out of reach of children. If swallowed, get medical help or contact a Poison Control Center right away.

Directions

Remove wipe by opening the adhesive label and pulling wipe from the center.
Replace adhesive label to close.

Children under 6 years of age should be supervised when using products.

Other information

Store in dry, cool place away from direct sunlight.

May discolor certain fabrics or surfaces

Inactive ingredients

Water, Aloe Barbadensis, Glycerin, Tocopheryl Acetate,

Package Label - Principal Display Panel

50 PC NDC: 80467-111-11